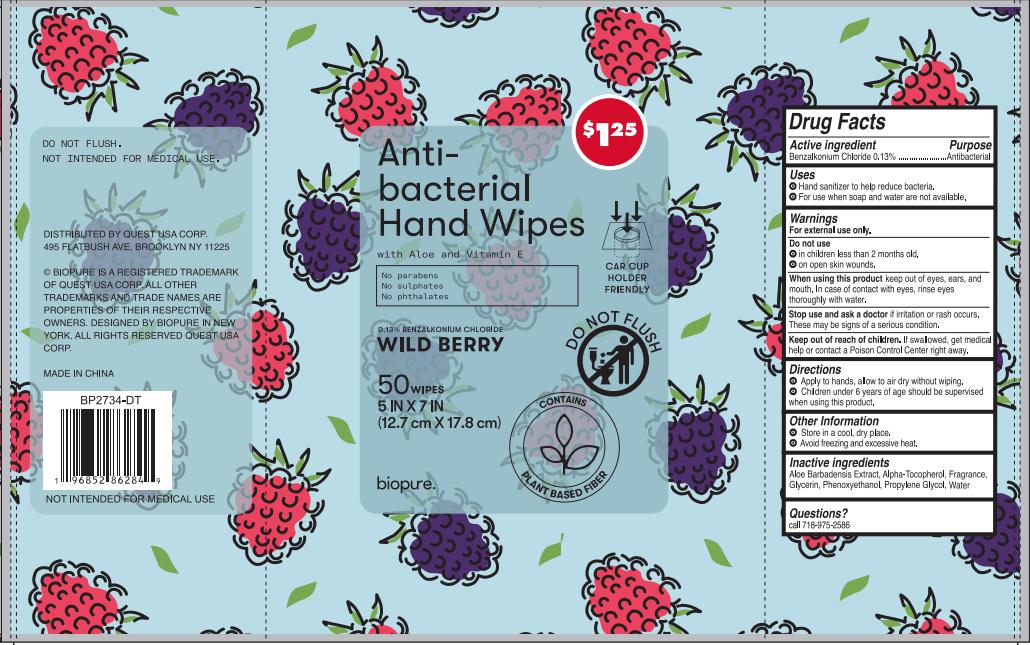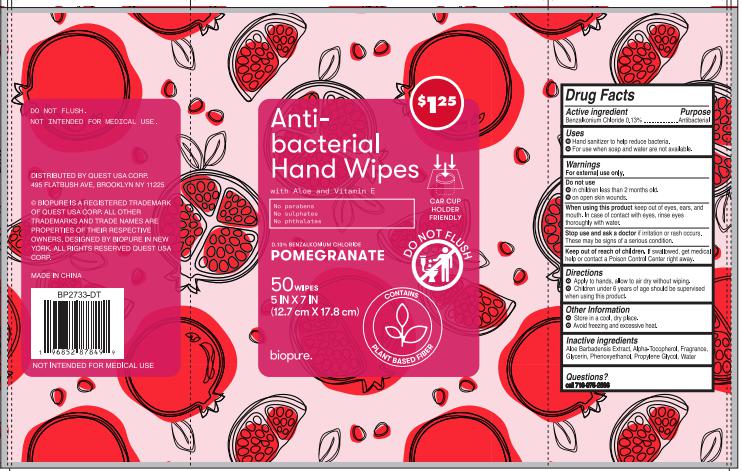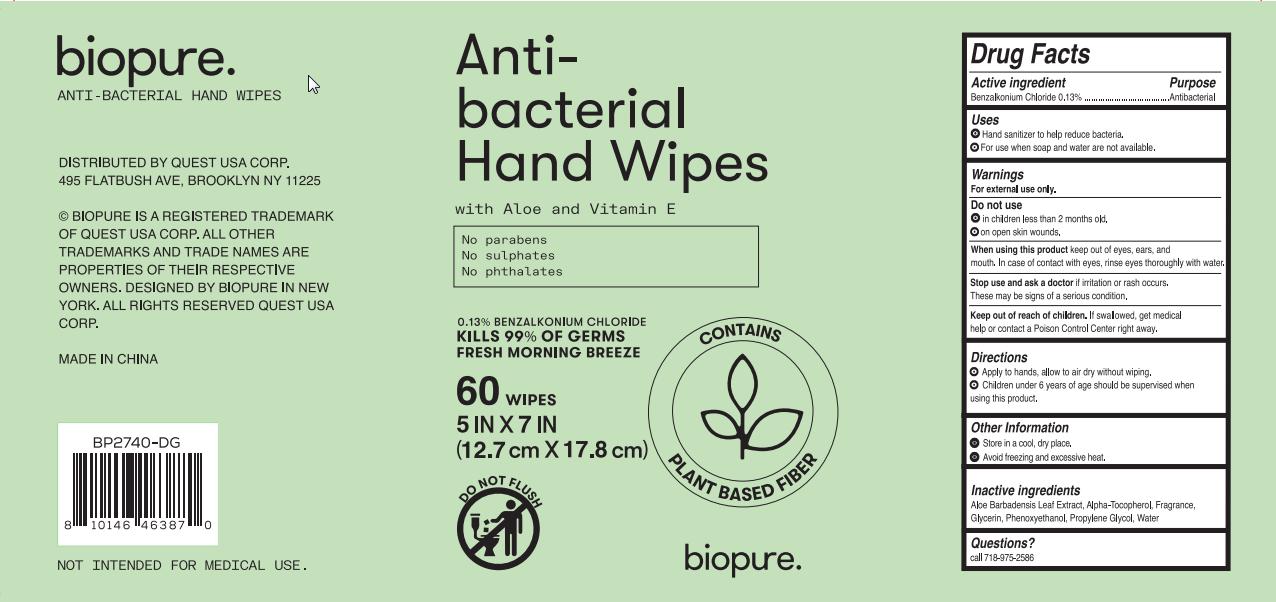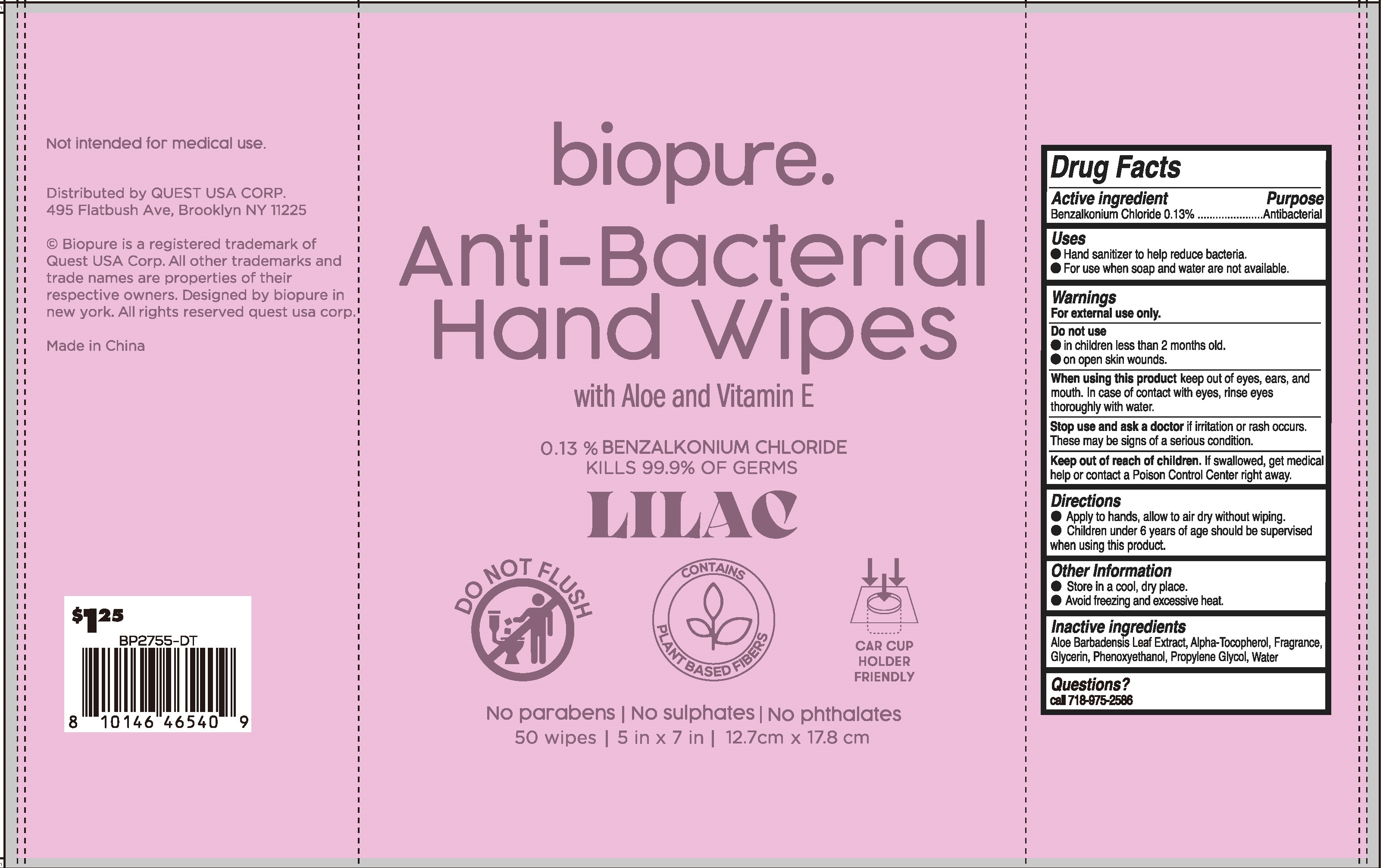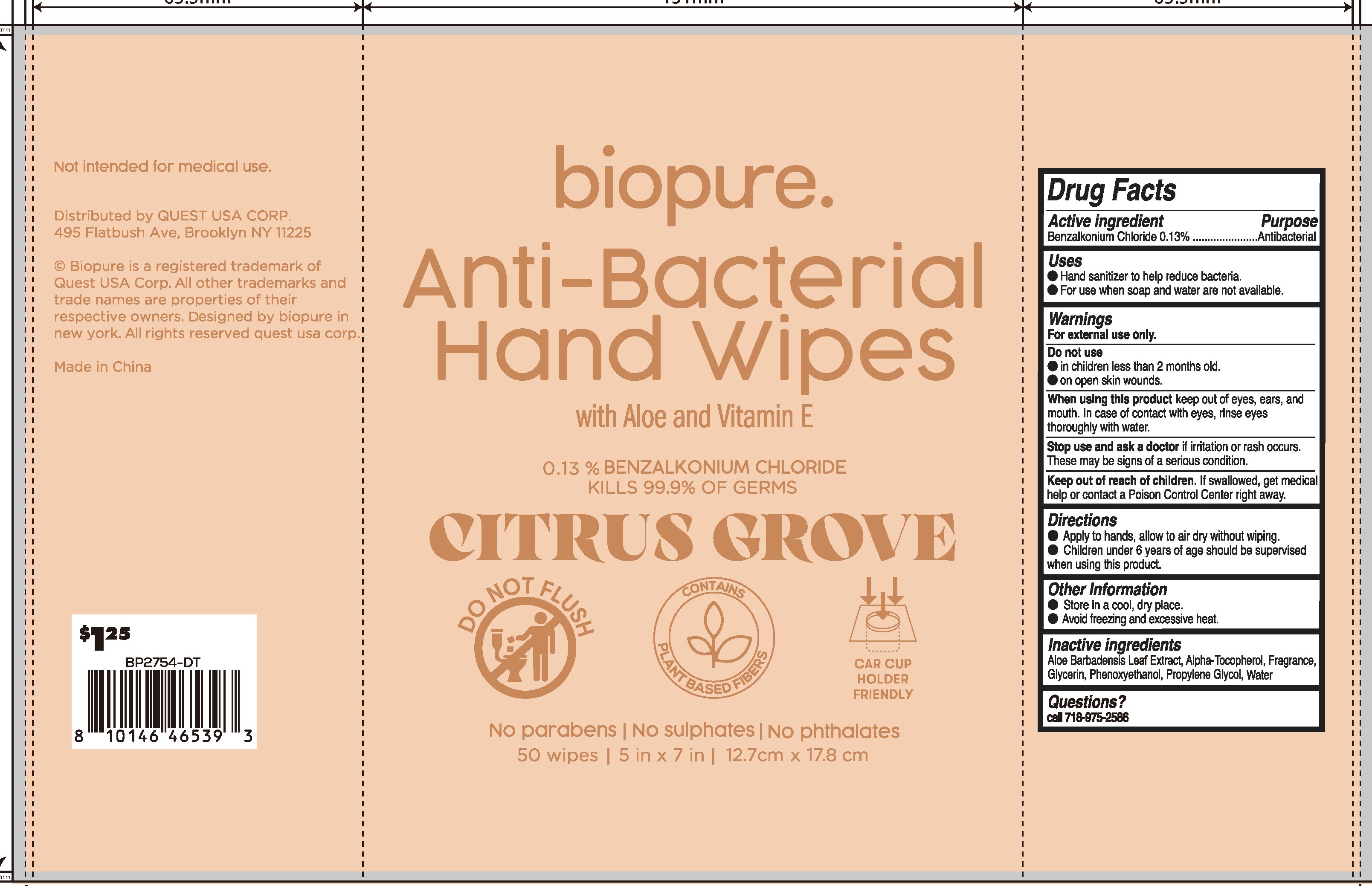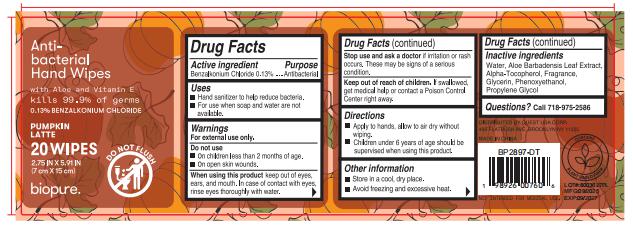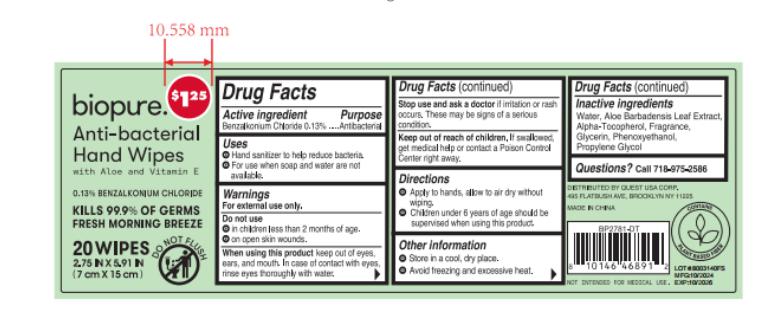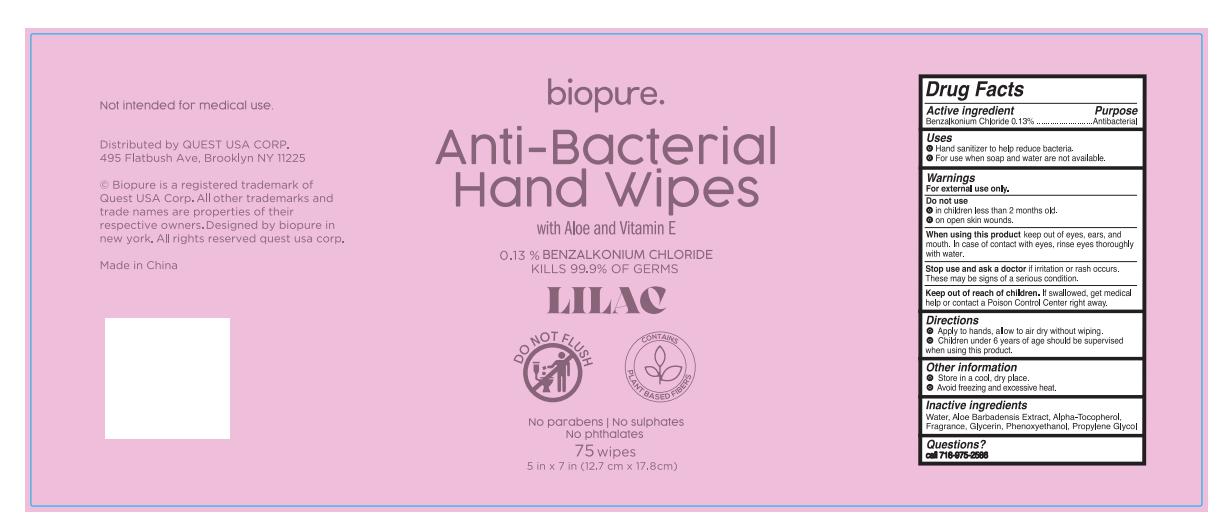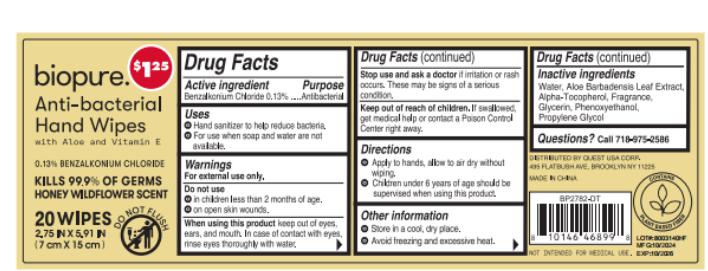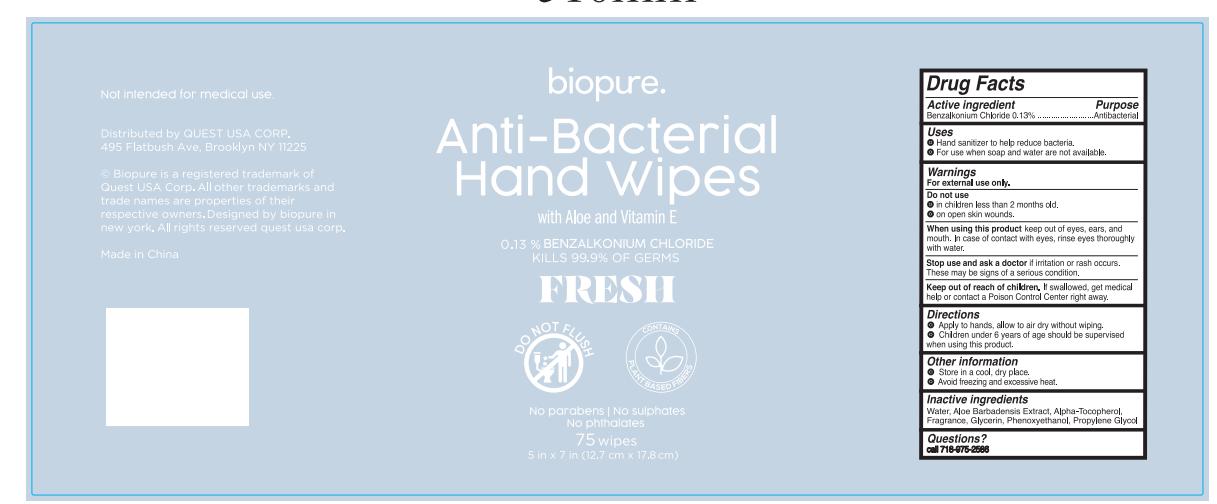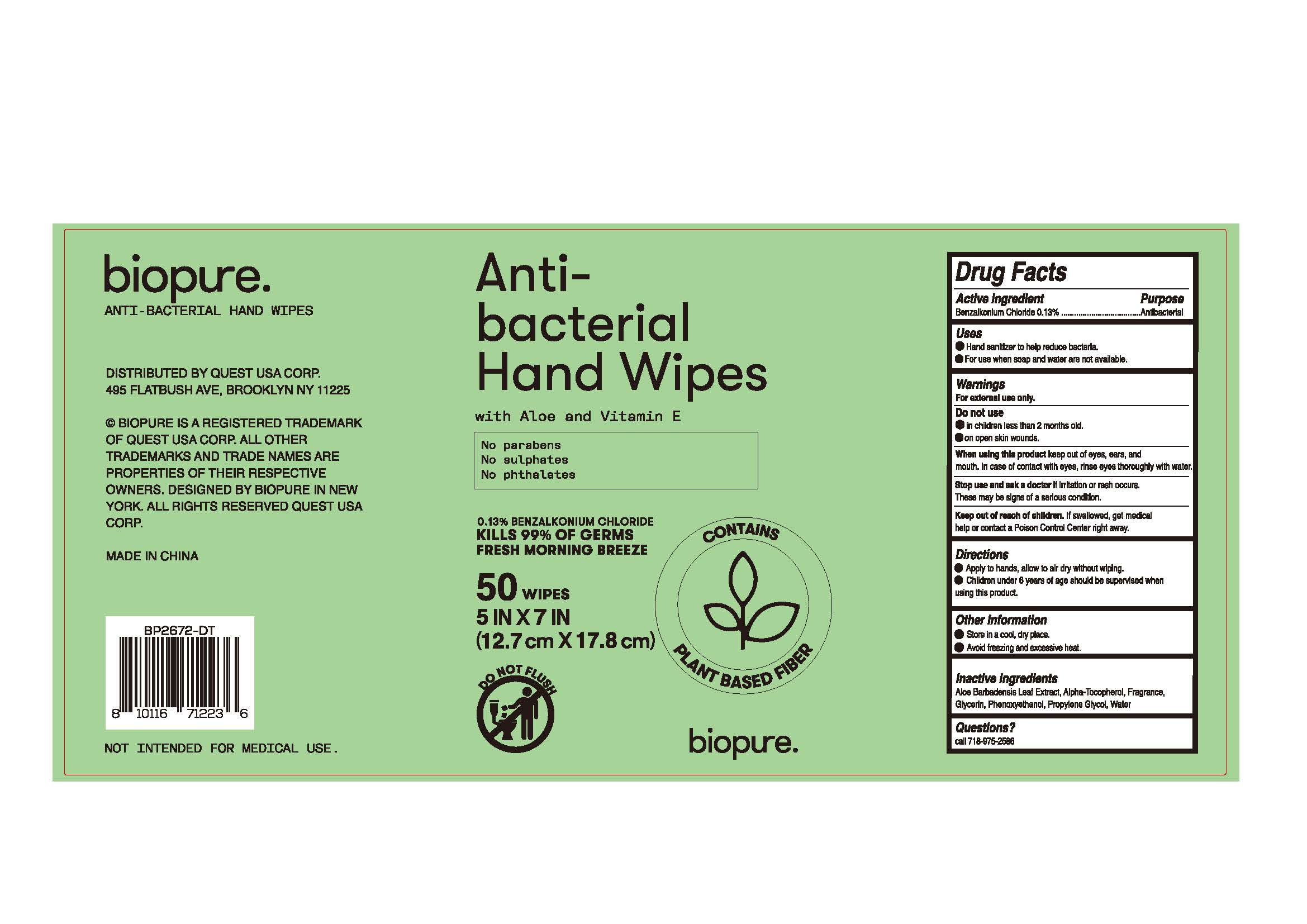 DRUG LABEL: BIOPURE 50CT ANTI BACTERIAL HAND WIPES
NDC: 79794-800 | Form: CLOTH
Manufacturer: Zhejiang Furuisen Spunlaced Nonwovens Co., Ltd.
Category: otc | Type: HUMAN OTC DRUG LABEL
Date: 20250930

ACTIVE INGREDIENTS: BENZALKONIUM CHLORIDE 0.13 g/100 1
INACTIVE INGREDIENTS: PROPYLENE GLYCOL; .ALPHA.-TOCOPHEROL, DL-; ALOE VERA LEAF; GLYCERIN; PHENOXYETHANOL; WATER

79794-800

Active ingredient

Benzalkonium Chloride 0.13%

Purpose

Antibacterial

Uses

●Hand sanitizer to help reduce bacteria

●For use when soap and water not available.

Warnings

For external use only.

Do not use

●in children less than 2 months old.

●on open skin wounds

When using this product

keep out of eyes, ears, and mouth. In case of contact with eyes, rinse eyes thoroughly with water.

Stop use and ask a doctor

if irritation or rash occurs.

These may be signs of a serious condition

Keep out of reach of children.

If swallowed. get medical help or contact a Poison Control Center right away.

Directions

●Apply to hands, allow to air dry without wiping.
●Children under 6 years of age should be supervised when using this product

Other Information

●Store in a cool, dry place.

●Avoid freezing and excessive heat.

Inactive ingredients

Aloe Barbadensis Leaf Extract, Alpha-Tocopherol, Fragrance, Glycerin, Phenoxyethanol, Propylene Glycol, Water

Question?

Call 718-975-2586